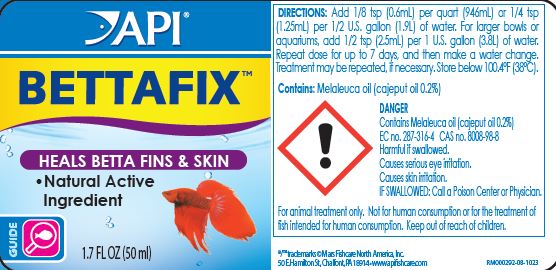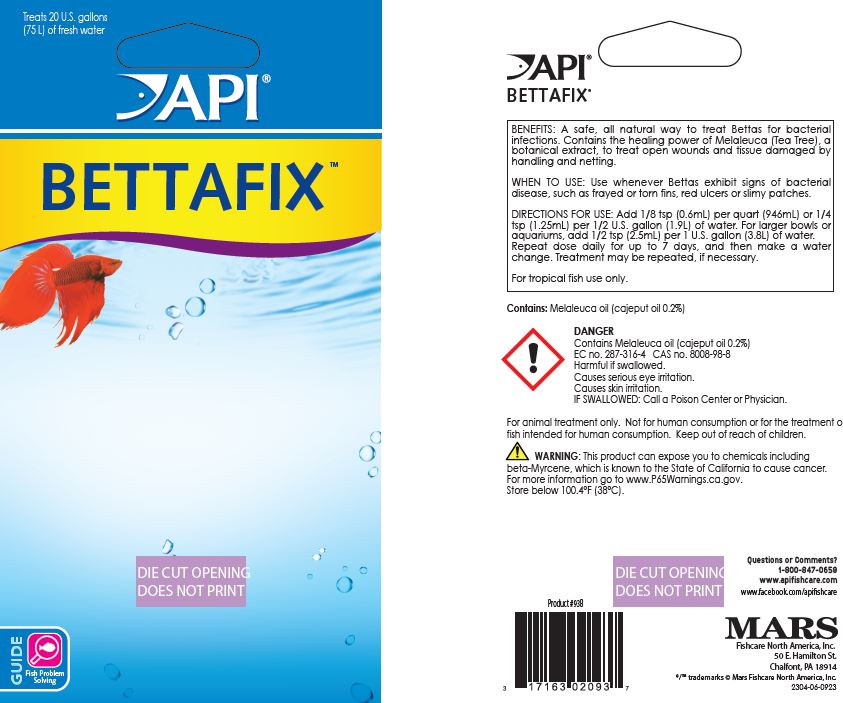 DRUG LABEL: API BettaFix
NDC: 17163-093 | Form: LIQUID
Manufacturer: MARS FISHCARE NORTH AMERICA, INC.
Category: animal | Type: OTC ANIMAL DRUG LABEL
Date: 20240410

ACTIVE INGREDIENTS: CAJUPUT OIL 0.2 g/100 mL

Drug Label

DESCRIPTION

BENEFITS:

A safe, all natural way to treat Bettas for bacterial infections.

Contains the healing power of Melaleuca (Tea Tree), a botanical extract, to treat open wounds and tissue damage by handling and netting.

INDICATIONS AND USAGE

WHEN TO USE:

Use whenever Bettas exhibit signs of bacterial disease, such as frayed or torn fins, red ulcers or slimy patches.

DOSAGE AND ADMINISTRATION

DIRECTIONS FOR USE:

Add 1/8 tsp (0.6mL) per quart (946mL) or 1/4 tsp. (1.25mL) per 1/2 U.S. gallon (1.9L) of water.

For larger bowls or aquariums, add 1/2 teaspoonful (2.5 ml) per 1 U.S. gallon (3.8 L) of water.

Repeat dose daily for up to 7 days, and then make a water change.

Treatment may be repeated, if necessary. Store below 100.4ºF (38ºC).

For tropical fish use only.

ACTIVE INGREDIENT

Contains: Melaleuca oil (cajeput oil 0.2%)

USER SAFETY WARNINGS

!

DANGER

Contains Melaleuca oil (cajeput oil 0.2%)

EC no. 287-316-4 CAS n. 8008-98-8

Harmful if swallowed.

Causes serious eye irritation.

Causes skin irritation.

IF SWALLOWED: Call a Poison Center or Physician.

For animal treatment only. Not for human consumption or for treatment of fish intended for human consumption. Keep out of reach of children.

! WARNING: This product can expose you to chemicals including beta-Myrcene, which is known to the State of California to cause cancer. For more information go to www.P65Warnings.ca.gov.

Store below 100°F (38ºC).